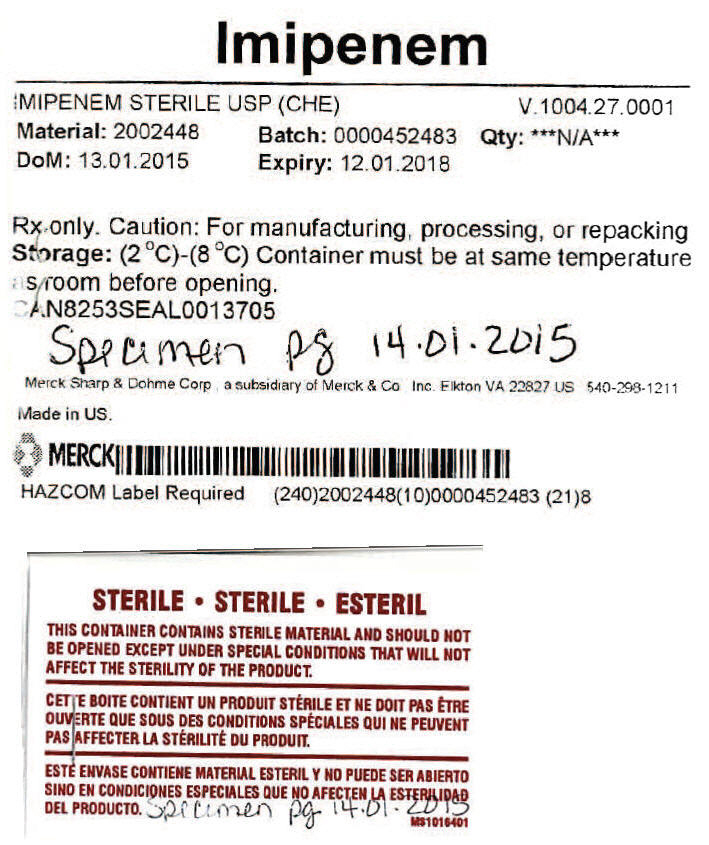 DRUG LABEL: Imipenem
NDC: 69806-0093 | Form: POWDER
Manufacturer: Merck Sharp & Dohme Corp.
Category: other | Type: BULK INGREDIENT
Date: 20171211

ACTIVE INGREDIENTS: IMIPENEM 1 kg/1 kg

Imipenem

PRINCIPAL DISPLAY PANEL - Shipping Label

Imipenem

IMIPENEM STERILE USP (CHE)
V.1004.27.0001

Material: 2002448
DoM: 13.01.2015

Batch: 0000452483
Expiry: 12.01.2018

Qty: ***N/A***

Rx only. Caution: For manufacturing, processing, or repacking
Storage: (2 °C)-(8 °C) Container must be at same temperature
as room before opening.
CAN8253SEAL0013705

Merck Sharp & Dohme Corp a subsidiary of Merck & Co Inc. Elkton VA 22827 US 540-298-1211

Made in US.

MERCK

HAZCOM Label Required

STERILE •
THIS CONTAINER CONTAINS STERILE MATERIAL AND SHOULD NOT
BE OPENED EXCEPT UNDER SPECIAL CONDITIONS THAT WILL NOT
AFFECT THE STERILITY OF THE PRODUCT.

MS1016401